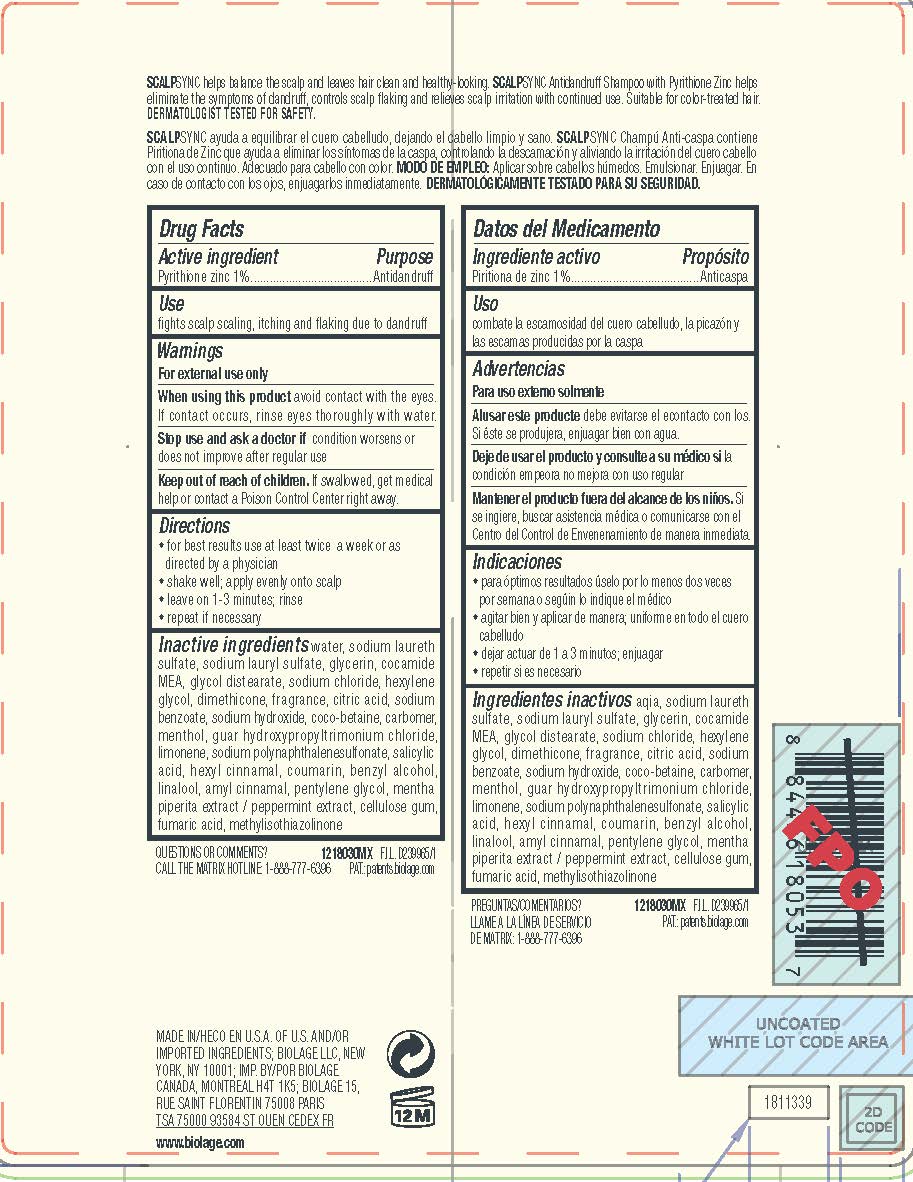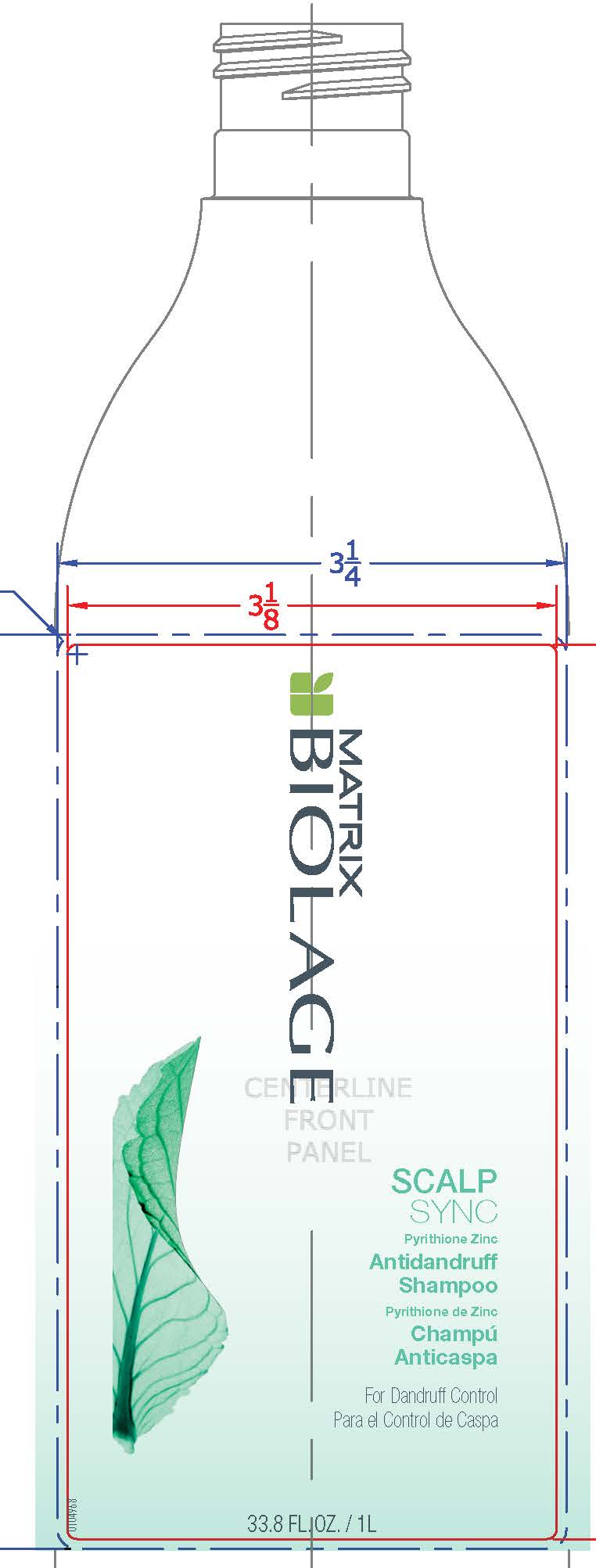 DRUG LABEL: Matrix Biolage ScalpSync Antidandruff
NDC: 49967-052 | Form: SHAMPOO
Manufacturer: L'Oreal USA Products Inc
Category: otc | Type: HUMAN OTC DRUG LABEL
Date: 20240718

ACTIVE INGREDIENTS: PYRITHIONE ZINC 10 mg/1 mL
INACTIVE INGREDIENTS: WATER; SODIUM LAURETH SULFATE; SODIUM LAURYL SULFATE; GLYCERIN; COCO MONOETHANOLAMIDE; GLYCOL DISTEARATE; SODIUM CHLORIDE; HEXYLENE GLYCOL; DIMETHICONE; CITRIC ACID MONOHYDRATE; SODIUM BENZOATE; SODIUM HYDROXIDE; COCO-BETAINE; CARBOMER HOMOPOLYMER, UNSPECIFIED TYPE; MENTHOL; GUAR HYDROXYPROPYLTRIMONIUM CHLORIDE (1.7 SUBSTITUENTS PER SACCHARIDE); LIMONENE, (+)-; SALICYLIC ACID; .ALPHA.-HEXYLCINNAMALDEHYDE; COUMARIN; BENZYL ALCOHOL; LINALOOL, (+/-)-; .ALPHA.-AMYLCINNAMALDEHYDE; PENTYLENE GLYCOL; MENTHA X PIPERITA WHOLE; CARBOXYMETHYLCELLULOSE SODIUM, UNSPECIFIED; FUMARIC ACID; METHYLISOTHIAZOLINONE

Drug Facts

Active ingredient

Pyrithione zinc 1%

Purpose

Antidandruff

Use

fights scalp scaling, itching and flaking due to dandruff

Warnings

For external use only

When using this product

avoid contact with the eyes. If contact occurs, rinse eyes thoroughly with water.

Stop use and ask a doctor if

condition worsens or does not improve after regular use

Keep out of reach of children.

If swallowed, get medical help or contact a Poison Control Center right away.

Directions

- for best results use at least twice a week or as directed by a physician

- shake well; apply evenly onto scalp

- leave on 1 - 3 minutes; rinse

- repeat if necessary

Inactive ingredients

water, sodium laureth sulfate, sodium lauryl sulfate, glycerin, cocamide MEA, glycol distearate, sodium chloride, hexylene glycol, dimethicone, fragrance, citric acid, sodium benzoate, sodium hydroxide, coco-betaine, carbomer, menthol, guar hydroxypropyltrimonium chloride, limonene, sodium polynaphthalenesulfonate, salicylic acid, hexyl cinnamal, coumarin, benzyl alcohol, linalool, amyl cinnamal, pentylene glycol, mentha piperita (peppermint) extract, cellulose gum, fumaric acid, methylisothiazolinone